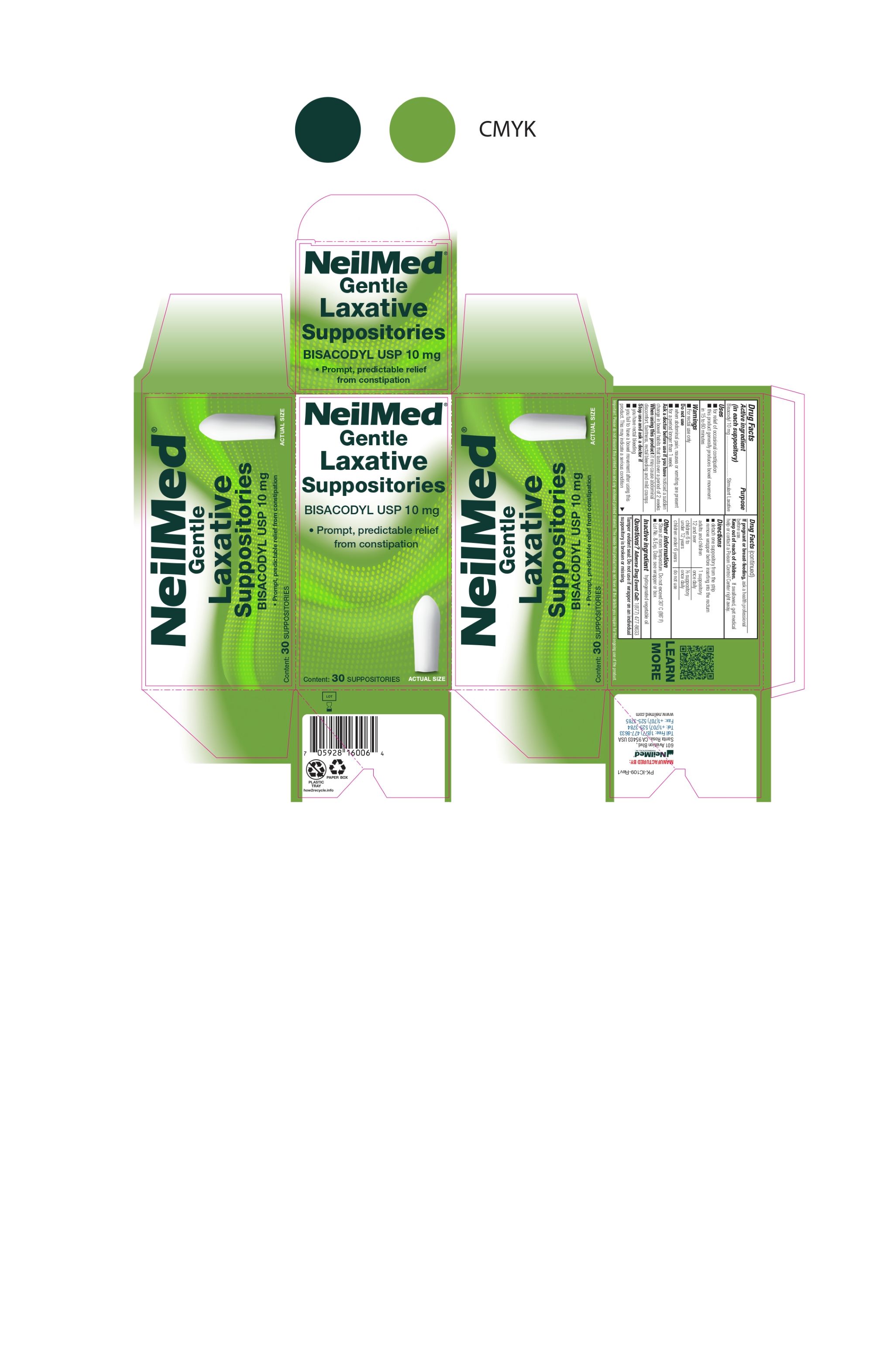 DRUG LABEL: Gentle Laxative Bisacodyl
NDC: 13709-321 | Form: SUPPOSITORY
Manufacturer: NeilMed Pharmaceuticals Inc
Category: otc | Type: HUMAN OTC DRUG LABEL
Date: 20250117

ACTIVE INGREDIENTS: BISACODYL 10 mg/1 1
INACTIVE INGREDIENTS: PALM KERNEL OIL

NeilMed Gentle Laxative Suppositories Bisacodyl USP 10mg

Drug Facts : Active ingredient

(in each suppository)
Bisacodyl 10 mg

Drug facts

Purpose
Bisacodyl 10 mg ................................. Stimulant Laxative

Uses

■ for relief of occasional constipation
■ this product generally produces bowel movement in 15 to 60 minutes

Warnings

■ For rectal use only

Do not use

■ when abdominal pain, nausea or vomiting are present
■ for a period longer than 1 week

Ask a doctor before use

if you have noticed a sudden change in bowel habits that lasts over a period of 2 weeks

When using this product

it may cause abdominal discomfort, faintness, rectal bleeding and mild cramps

Stop use and ask a doctor if

■ you have rectal bleeding
■ you fail to have a bowel movement after using this product. This may indicate a serious condition

If pregnant or breast-feeding,

ask a health professional before use.

Keep out of reach of children.

If swallowed, get medical help or contact a Poison Control Center right away.

Directions

■ detach one suppository from the strip
■ remove wrapper before inserting into the rectum

adults and children 12 and over : 1 suppository once daily
children 6 to under 12 years : ½ suppository once daily
children under 6 years : do not use

Other information

■ Store at room temperature. Do not exceed 30° C (86° F)
■ Lot No. & Exp. Date: see wrapper or box

Inactive ingredient

hydrogenated vegetable oil

Questions?

Adverse Drug Event Call: 1(877) 477-8633

Tamper evident seal:

Do not use if wrapper on an individual suppository is broken or missing.

INTENDED USE OF THE DEVICE

Prompt, predictable relief from constipation